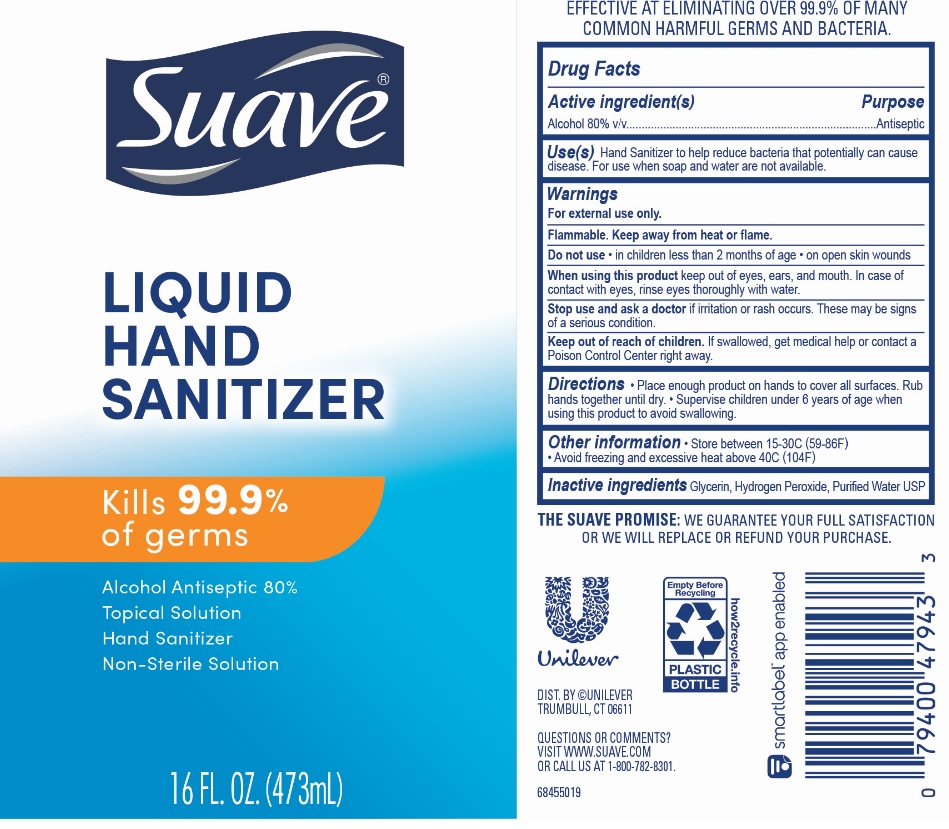 DRUG LABEL: Suave
NDC: 64942-1770 | Form: LIQUID
Manufacturer: Conopco Inc. d/b/a/ Unilever
Category: otc | Type: HUMAN OTC DRUG LABEL
Date: 20221207

ACTIVE INGREDIENTS: ALCOHOL 800 mg/1 mL
INACTIVE INGREDIENTS: WATER; GLYCERIN; HYDROGEN PEROXIDE

Suave Liquid Hand Sanitize

SUAVE LIQUID HAND SANITIZER - Alcohol liquid

Suave Liquid Hand Sanitizer

Drug Facts

Active ingredient

Alcohol (80%)

Purpose

Antiseptic

Use(s)

Hand Sanitizer to help reduce bacteria that potentially can cause disease. For use when soap and water are not available

Warnings

For external use only
Flammable. Keep away from heat or flame
Do not use • in children less than 2 months of age • on open skin wounds
When using this product keep out of eyes, ears and mouth. In case of contact with eyes, rinse eyes thoroughly with water.
Stop use and ask a doctor if irritation or rash occurs. These may be signs of a serious condition.

.

• Keep out of reach of children.
If swallowed, get medical help or contact a Poison Control Center right away.

Directions

• Place enough product on hands to cover all surfaces. Rub hands together until dry. • Supervise children under 6 years of age when using this product to avoid swallowing.

Other information

• Store between 15-30C (59-86F)
• Avoid freezing and excessive heat above 40C (104F)

Inactive ingredients

Glycerin, Hydrogen Peroxide, Purified Water USP

Questions?

Call us at 1-800-782-8301.